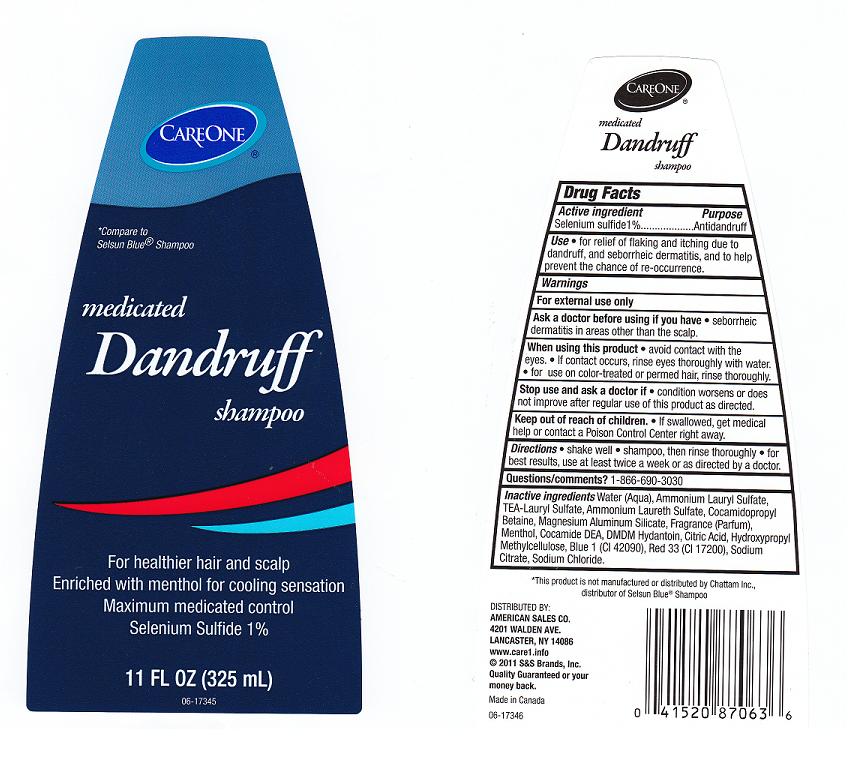 DRUG LABEL: MEDICATED DANDRUFF
NDC: 41520-614 | Form: SHAMPOO
Manufacturer: AMERICAN SALES COMPANY
Category: otc | Type: HUMAN OTC DRUG LABEL
Date: 20110819

ACTIVE INGREDIENTS: SELENIUM SULFIDE 1 mL/100 mL
INACTIVE INGREDIENTS: WATER; AMMONIUM LAURYL SULFATE; TROLAMINE LAURYL SULFATE; COCAMIDOPROPYL BETAINE; MAGNESIUM ALUMINUM SILICATE; MENTHOL; COCO DIETHANOLAMIDE; DMDM HYDANTOIN; CITRIC ACID MONOHYDRATE; HYPROMELLOSES; FD&C BLUE NO. 1; D&C RED NO. 33; SODIUM CITRATE; SODIUM CHLORIDE; AMMONIUM LAURETH-2 SULFATE

DRUG FACTS

ACTIVE INGREDIENT

SELENIUM SULFIDE 1%

PURPOSE

ANTI-DANDRUFF

USES

FOR RELIEF OF FLAKING AND ITCHING DUE TO DANDRUFF, AND SEBORRHEIC DERMATITIS, AND TO HELP PREVENT THE CHANCE OF RE-OCCURENCE.

WARNINGS

FOR EXTERNAL USE ONLY.

ASK A DOCTOR BEFORE USING IF YOU HAVE

SEBORRHEIC DERMATITIS IN AREAS OTHER THAN THE SCALP.

WHEN USING THIS PRODUCT

AVOID CONTACT WITH THE EYES.IF CONTACT OCCURS, RINSE EYES THOROUGHLY WITH WATER. FOR USE ON COLOR-TREATED OR PERMED HAIR, RINSE THOROUGHLY.

STOP USE AND ASK A DOCTOR IF

CONDITION WORSENS OR DOES NOT IMPROVE AFTER REGULAR USE OF THIS PRODUCT AS DIRECTED.

KEEP OUT OF REACH OF CHILDREN

IF SWALLOWED, GET MEDICAL HELP OR CONTACT A POISON CONTROL CENTER RIGHT AWAY.

DIRECTIONS

SHAKE WELL. SHAMPOO, THEN RINSE THOROUGHLY. FOR BEST RESULTS, USE AT LEAST TWICE A WEEK OR AS DIRECTED BY A DOCTOR.

QUESTIONS/COMMENTS?

1-866-690-3030

INACTIVE INGREDIENTS

WATER (AQUA), AMMONIUM LAURYL SULFATE, TEA-LAURYL SULFATE, AMMONIUM LAURETH SULFATE, COCAMIDOPROPYL BETAINE, MAGNESIUM ALUMINUM SILICATE, FRAGRANCE, MENTHOL, COCAMIDE DEA, DMDM HYDANTOIN, CITRIC ACID, HYDROXYPROPYL METHYLCELLULOSE, BLUE 1, RED 33, SODIUM CITRATE, SODIUM CHLORIDE